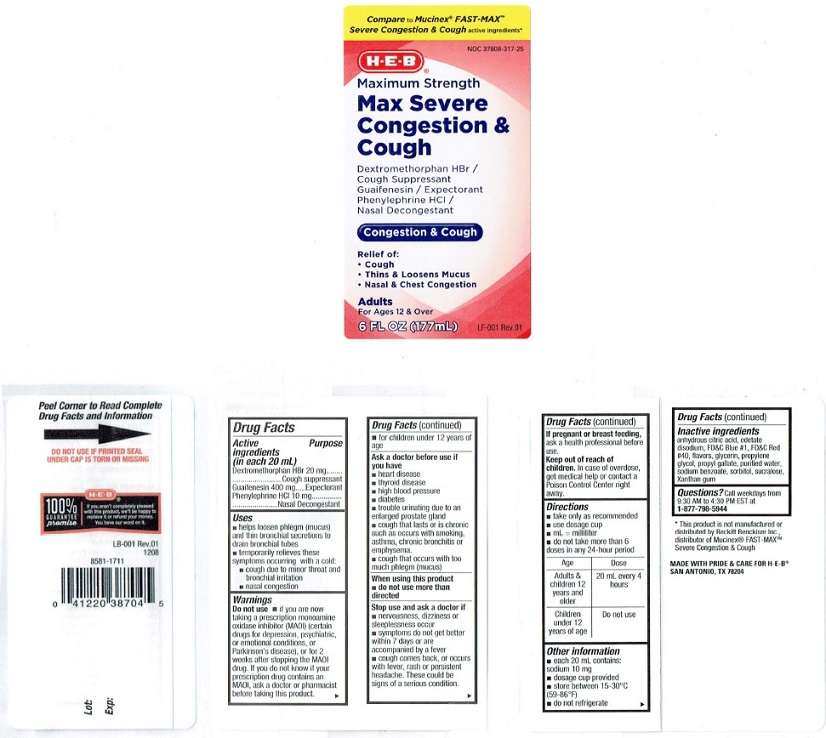 DRUG LABEL: H E B MAX SEVERE CONGESTION and COUGH
NDC: 37808-317 | Form: LIQUID
Manufacturer: H E B
Category: otc | Type: HUMAN OTC DRUG LABEL
Date: 20231229

ACTIVE INGREDIENTS: DEXTROMETHORPHAN HYDROBROMIDE 20 mg/20 mL; GUAIFENESIN 400 mg/20 mL; PHENYLEPHRINE HYDROCHLORIDE 10 mg/20 mL
INACTIVE INGREDIENTS: ANHYDROUS CITRIC ACID; EDETATE DISODIUM; FD&C BLUE NO. 1; FD&C RED NO. 40; GLYCERIN; PROPYLENE GLYCOL; PROPYL GALLATE; WATER; SODIUM BENZOATE; SORBITOL; SUCRALOSE; XANTHAN GUM

Drug Facts

Active ingredients (in each 20 mL)
Dextromethorphan HBr 20 mg
Guaifenesin 400 mg
Phenylephrine HCL 10 mg

Purpose

Dextromethorphan HBr ... Cough suppressant
Guaifenesin ....................Expectorant
Phenylephrine HCL ..........Nasal Decongestant

Uses
• helps loosen phlegm (mucus)
and thin bronchial secretions to
drain bronchial tubes
• temporarily relieves these
symploms occurring with a cold:
• cough due to minor throat and
bronchial irritation
• nasal congestion

Warnings
Do not use • if you are now
taking a prescription monoamine
oxiclase inhibitor (MAOI) (certain
drugs for depression. psychiatric.
or emotional conditions, or
Parkinson's disease), or for 2
weeks after stopping the MAOI
drug. If you do not know if your
prescription drug contains an
MAOI, ask a doctor or pharmacist
before taking this product.
• for children under 12 years of
age

Ask a doctor before use if
you have
• heart disease
• thyroid disease
• high blood pressure
• diabetes
• trouble urinating due to an
enlarged prostate gland
• cough that lasts or is chronic
such as occurs with smoking,
asthma, chronic bronchitis or
emphysema.
• cough that occurs with too
much phlegm (mucus)

When using this product
• do not use more than
directed

Stop use and ask a doctor if
• nervousness, dizziness or
sleeplessness occur
• symptoms do not get better
within 7 days or are
accompanied by a fever
• cough comes back, or occurs
with fever, rash or persistent
headache. These could be
signs of a serious condition.

If pregnant or breast feeding,

ask a health professional before use.

Keep out of reach of
children. In case of overdose,
get medical help or contact a
Poison Control Center right
away.

Directions
• take only as recommended
• use dosage cup
• mL = milliliter
• do not take more than 6
doses in any 24-hour period

Age Dose

Adults & 20 ml every 4
children 12 hours
years and
older

Children Do not use
under 12
years of age

Other information

- each 20 mL contains: sodium 10 mg
- dosage cup provided
- store between 15-30° C (59-86° F)
- do not refrigerate

Inactive ingredients
anhydrous cilric acid, edetate
disodium, FD&C Blue #1, FD&C Red
#40. flavors. glycerin, propylene
glycol, propyl gallate, purified water,
sodium benzoate, sorbitol, sucralose,
Xanthan gum

QUESTIONS

Questions? Call weekdays from 9:30 AM to 4:30 PM EST at
1-877-798-5944

Product Label

Compare to Mucinex® FAST-MAX™

Severe Congestion and Cough active ingredients*

NDC 37808-317-25
H-E-B®

Maximum Strength

Max Severe
Congestion &
Cough
Dextromethorphan HBr /
Cough Suppressant
Guaifenesin / Expectorant
Phenylephrine HCI /
Nasal Decongestant

Congestion & Cough

Relief of:
• Cough
• Thins & Loosens Mucus
• Nasal & Chest Congestion

Adults

For Ages 12 & Over

6 FL OZ (177mL)

LF 001 Rev.01

MADE WITH PRIDE AND CARE FOR H-E-B®

SAN ANTONIO, TEXAS, 782044

Peel Corner to Read Complete
Drug Facts and Information →

DO NOT USE IF PRINTED SEAL

UNDER CAP IS TORN OR MISSING

H-E-B®

100%
GUARANTEE
promise

If you aren't completely pleased
with this product, we'll be happy to
replace it or refund your money.
You have our word on it.

LB·001 Rev.01
1208
8581-1711

0 41220 38704 5
Lot:
Exp:

*This product is not manufactured or
distributed by Reckill Benckiser Inc..
distributor of Mucinex® FAST-MAXTM
Severe Congeslion &Cough

MADE WITH PRIDE & CARE FOR H·E-B®
SAN ANTONIO. TX 78204

res